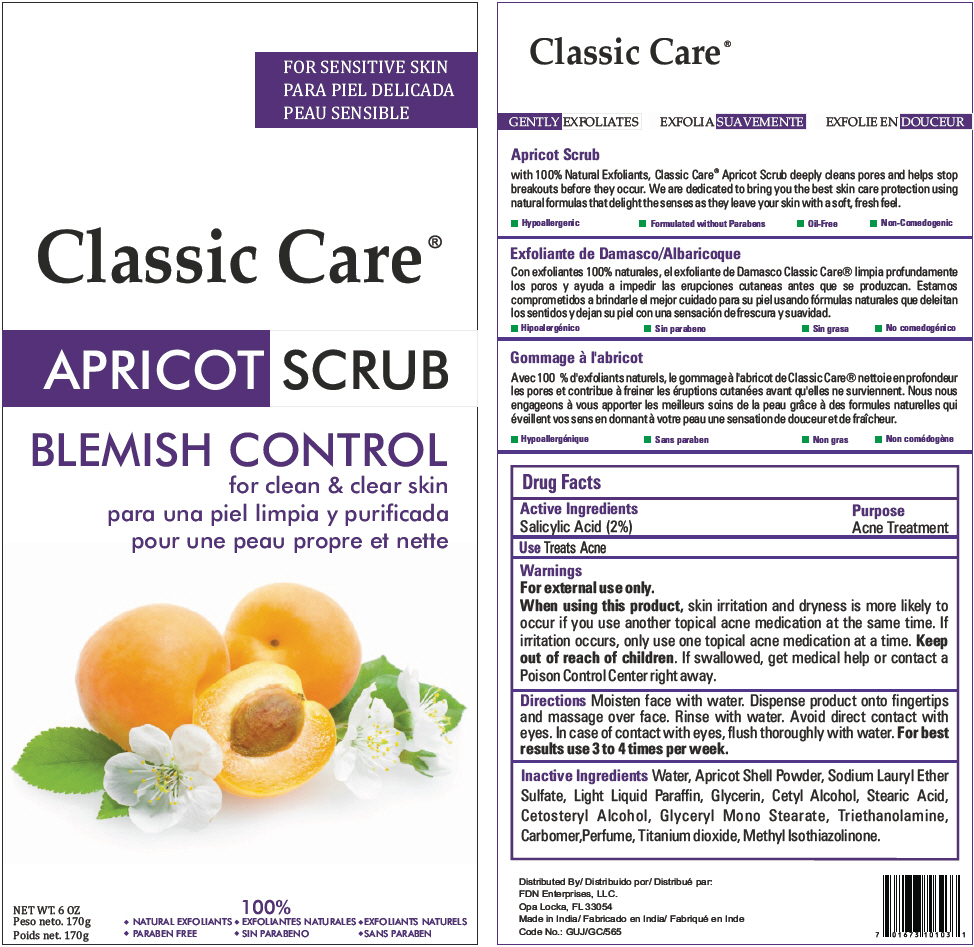 DRUG LABEL: Classic Care Apricot Scrub 
NDC: 60691-124 | Form: CREAM
Manufacturer: FDN Enterprises, LLC
Category: otc | Type: HUMAN OTC DRUG LABEL
Date: 20140328

ACTIVE INGREDIENTS: Salicylic Acid 2 g/100 g
INACTIVE INGREDIENTS: Water; Light Mineral Oil; Glycerin; Cetyl Alcohol; Stearic Acid; Cetostearyl Alcohol; Glyceryl Monostearate; Trolamine; Titanium dioxide; Methylisothiazolinone

Classic Care® Apricot Scrub
Blemish Control

Drug Facts

Active Ingredients

Salicylic Acid (2%)

Purpose

Acne Treatment

Use

Treats Acne

Warnings

For external use only.

When using this product, skin irritation and dryness is more likely to occur if you use another topical acne medication at the same time. If irritation occurs, only use one topical acne medication at a time.

Keep out of reach of children. If swallowed, get medical help or contact a Poison Control Center right away.

Directions

Moisten face with water. Dispense product onto fingertips and massage over face. Rinse with water. Avoid direct contact with eyes. In case of contact with eyes, flush thoroughly with water. For best results use 3 to 4 times per week.

Inactive Ingredients

Water, Apricot Shell Powder, Sodium Lauryl Ether Sulfate, Light Liquid Paraffin, Glycerin, Cetyl Alcohol, Stearic Acid, Cetosteryl Alcohol, Glyceryl Mono Stearate, Triethanolamine, Carbomer,Perfume, Titanium dioxide, Methyl Isothiazolinone.

Distributed By:
FDN Enterprises, LLC.
Opa Locka, FL 33054

PRINCIPAL DISPLAY PANEL - 170 g Tube Label

FOR SENSITIVE SKIN

Classic Care®

APRICOT SCRUB

BLEMISH CONTROL
for clean & clear skin

NET WT. 6 OZ

100%
♦ NATURAL EXFOLIANTS
♦ PARABEN FREE